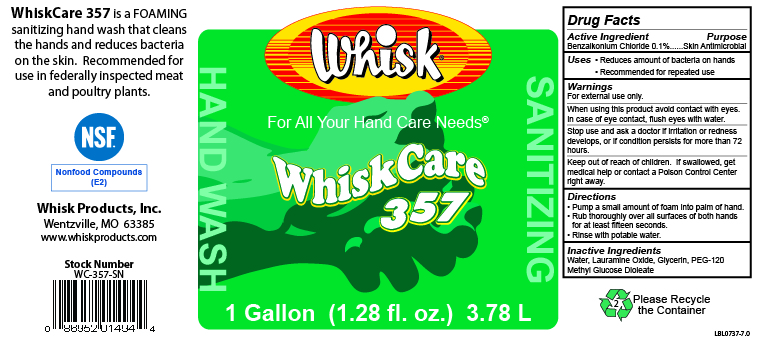 DRUG LABEL: WhiskCare 357
NDC: 65585-557 | Form: SOAP
Manufacturer: Whisk Products, Inc.
Category: otc | Type: HUMAN OTC DRUG LABEL
Date: 20250516

ACTIVE INGREDIENTS: BENZALKONIUM CHLORIDE 1 mg/1 mL
INACTIVE INGREDIENTS: GLYCERIN; LAURAMINE OXIDE; PEG-120 METHYL GLUCOSE DIOLEATE; WATER

WhiskCare 357

Active Ingredient

Benzalkonium Chloride 0.1%

Purpose

Skin Antimicrobial

Uses

- Reduces amount of bacteria on hand
- Recommended for repeated use

Warnings

For external use only.

When using this product avoid contact with eyes. In case of eye contact, flush eyes with water.

Stop use and ask a doctor if irritation or redness develops, or if condition persists for more than 72 hours.

Keep out of reach of children. If swallowed, get medical help or contact a Poison Control Center right away.

Directions

- Pump a small amount of foam into palm of hand.
- Rub thoroughly over all surfaces of both hands for at least fifteen seconds.
- Rinse with potable water.

Inactive Ingredients

Water, Lauramine Oxide, Glycerin, PEG-120 Methyl Glucose Dioleate